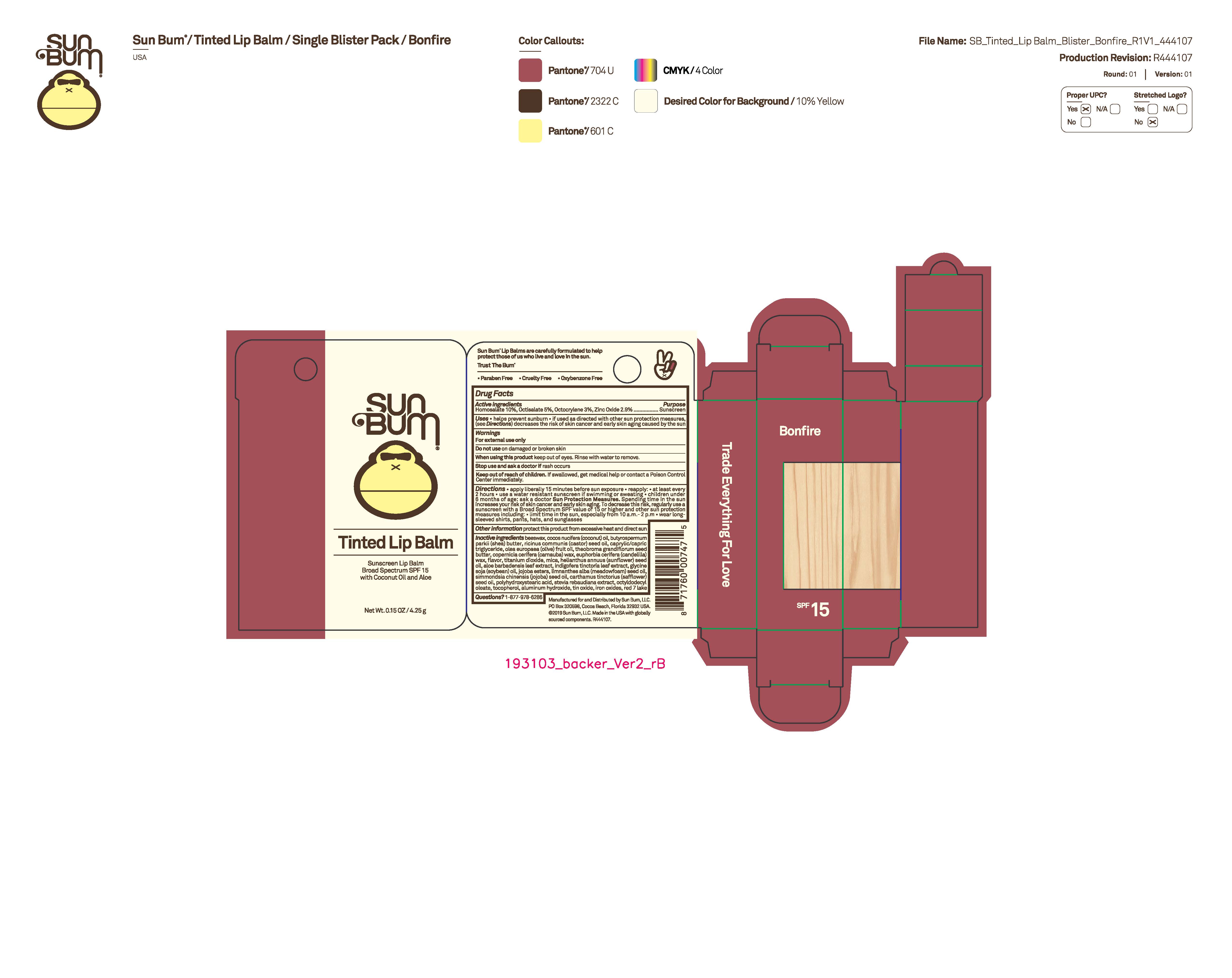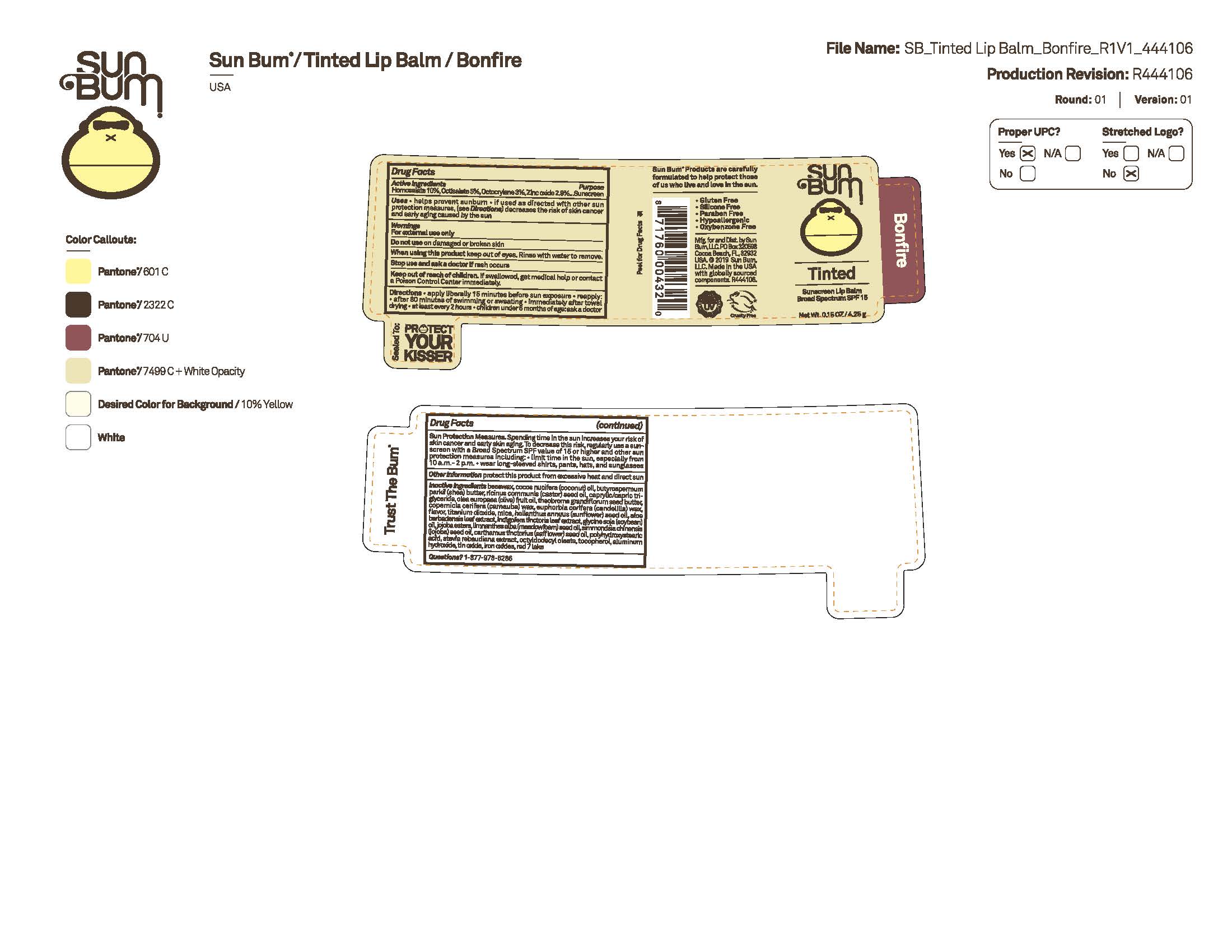 DRUG LABEL: Sun Bum Tinted Sunscreen Lip Balm Broad Spectrum SPF 15 - Bonfire
NDC: 69039-736 | Form: STICK
Manufacturer: Sun Bum, LLC
Category: otc | Type: HUMAN OTC DRUG LABEL
Date: 20250814

ACTIVE INGREDIENTS: OCTOCRYLENE 30 mg/1 g; HOMOSALATE 100 mg/1 g; OCTISALATE 50 mg/1 g; ZINC OXIDE 29 mg/1 g
INACTIVE INGREDIENTS: BEESWAX; MICA; TOCOPHEROL; HYDROLYZED JOJOBA ESTERS; ALOE BARBADENSIS LEAF; SOYBEAN OIL; EUPHORBIA CERIFERA (CANDELILLA) WAX; ALUMINUM HYDROXIDE; OLEA EUROPAEA (OLIVE) FRUIT OIL; THEOBROMA GRANDIFLORUM SEED BUTTER; COPERNICIA CERIFERA (CARNAUBA) WAX; STEVIA REBAUDIUNA LEAF; BUTYROSPERMUM PARKII (SHEA) BUTTER; SIMMONDSIA CHINENSIS (JOJOBA) SEED OIL; POLYHYDROXYSTEARIC ACID (2300 MW); RICINUS COMMUNIS (CASTOR) SEED OIL; CAPRYLIC/CAPRIC TRIGLYCERIDE; TIN OXIDE; TITANIUM DIOXIDE; HELIANTHUS ANNUUS (SUNFLOWER) SEED OIL; CARTHAMUS TINCTORIUS (SAFFLOWER) SEED OIL; OCTYLDODECYL OLEATE; COCOS NUCIFERA (COCONUT) OIL; INDIGOFERA TINCTORIA LEAF; LIMNANTHES ALBA (MEADOWFOAM) SEED OIL; RED 7; FERRIC OXIDE RED

Sun Bum Tinted Sunscreen Lip Balm Broad Spectrum SPF 15 - Bonfire, Bonfire Carded

Active Ingredients

Homosalate 10%, Octisalate 5%, Octocrylene 3%, Zinc oxide 2.9%

Purpose

Sunscreen

Uses

• helps prevent sunburn • if used as directed with other sun protection measures, (see Directions) decreases the risk of skin cancer and early skin aging caused by the sun

Warnings

For external use only

Do not use on damaged or broken skin

When using this product keep out of eyes. Rinse with water to remove.

Stop use and ask a doctor if rash occurs

Keep out of reach of children. If swallowed, get medical help or contact a Poison Control Center immediately.

Warnings

Keep Out Of Reach Of Children

Directions

• apply liberally 15 minutes before sun exposure

• reapply: • after 80 minutes of swimming or sweating • immediately after towel drying • at least every 2 hours

• children under 6 months of age: ask a doctor

• Sun Protection Measures. Spending time in the sun increases your risk of skin cancer and early skin aging. To decrease this risk, regularly use a sunscreen with a Broad Spectrum SPF value of 15 or higher and other sun protection measures including:

• limit time in the sun, especially from 10 a.m.- 2 p.m.

• wear long-sleeved shirts, pants, hats and sunglasses

Directions

• apply liberally 15 minutes before sun exposure

Other Information

protect this product from excessive heat and direct sun

Bonfire and Bonfire Carded Inactive Ingredients

beeswax, cocos nucifera (coconut) oil, butyrospermum parkii (shea) butter, ricinus communis (castor) seed oil, caprylic/capric triglyceride, olea europaea (olive) fruit oil, theobroma grandiflorum seed butter, copernicia cerifera (carnauba) wax, euphorbia cerifera (candelilla) wax, flavor, titanium dioxide, mica, helianthus annuus (sunflower) seed oil, aloe barbadensis leaf extract, indigofera tinctoria leaf extract, glycine soja (soybean) oil, jojoba esters, limnanthes alba (meadowfoam) seed oil, simmondsia chinensis (jojoba) seed oil, carthamus tinctorius (safflower) seed oil, polyhydroxystearic acid, stevia rebaudiana extract, octyldodecyl oleate, tocopherol, aluminum hydroxide, tin oxide, iron oxides, red 7 lake

Questions?

1-877-978-6286